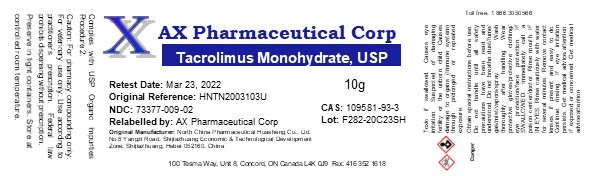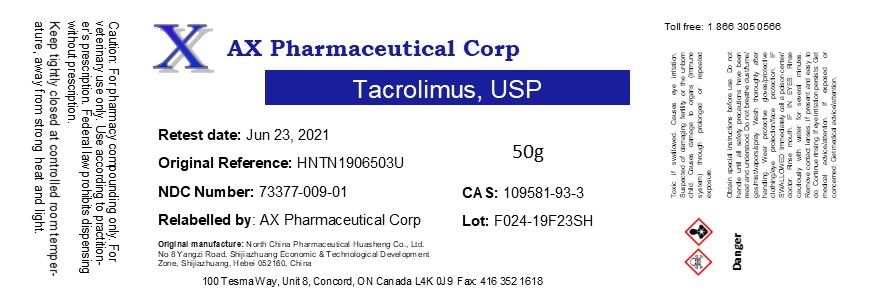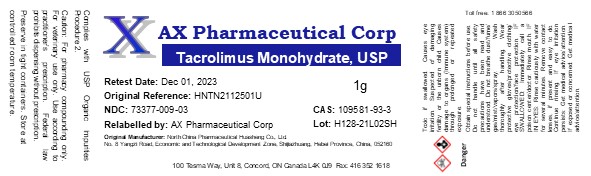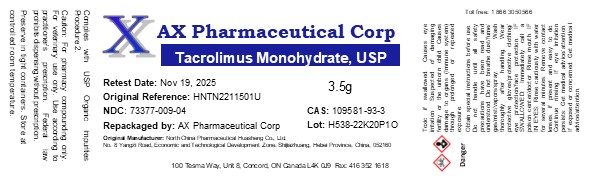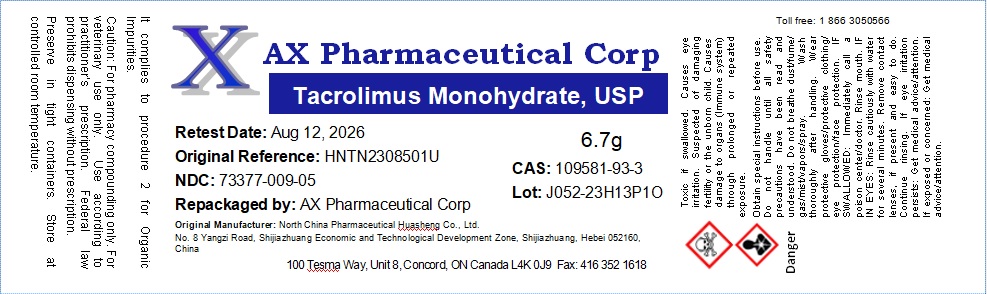 DRUG LABEL: Tacrolimus
NDC: 73377-009 | Form: POWDER
Manufacturer: AX Pharmaceutical Corp
Category: other | Type: BULK INGREDIENT - ANIMAL DRUG
Date: 20241202

ACTIVE INGREDIENTS: TACROLIMUS 1 g/1 g

Tacrolimus